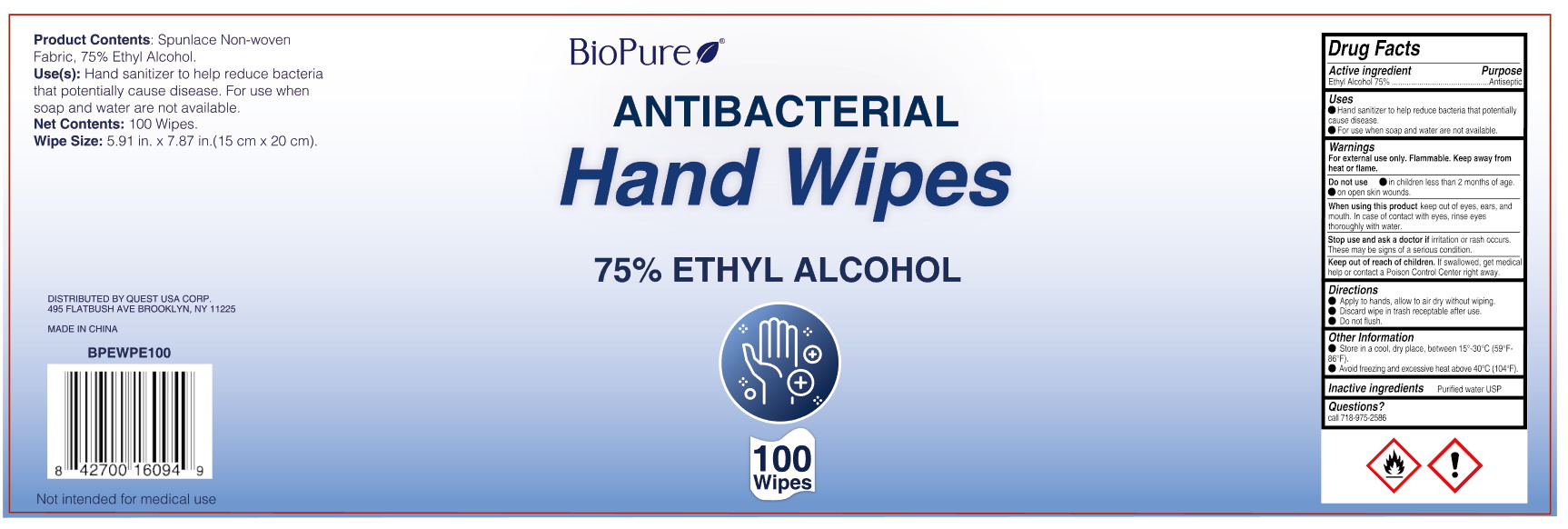 DRUG LABEL: BioPure 75% Alcohol Wipes
NDC: 78183-005 | Form: CLOTH
Manufacturer: Kunming Ansheng Industry & Trade Co., Ltd.
Category: otc | Type: HUMAN OTC DRUG LABEL
Date: 20200713

ACTIVE INGREDIENTS: ALCOHOL 0.75 U/1 U
INACTIVE INGREDIENTS: WATER

75% Alcohol Wipes (BioPure)

Active Ingredient(s)

Alcohol 75% v/v.

Purpose

Antibacterial;

Use

Hand sanitizer to help reduce bacterial that potentially casue disease.

Warnings

For external use only. Flammable. Keep away from heat or flame

Do not use

- in children less than 2 months of age
- on open skin wounds

When using this product do not use in or contact the eyes, ears, and mouth.
In case of contact with eyes, rinse eyes thoroughly with water.

Stop use and ask a doctor if irritation or rash occurs.
These may be sign of serious condition.

Keep out of reach of children. If swallowed, get medical help or contact a Poison Control Center right away.

Directions

- Apply to hands, allow to air dry without wiping.
- Discard wipe in trash receptable after use.
- Do not flush.

Inactive ingredients

Pure water; Spunlace Non-woven Fabric;

Other Information

- Keep in cool, dry place, between 15-30℃ (59-86℉).
- Avoid freezing and excessive heat above 40℃ (104℉).

Package Label - Principal Display Panel

100 wipes in 1 canister.

NDC: 78183-005-01;